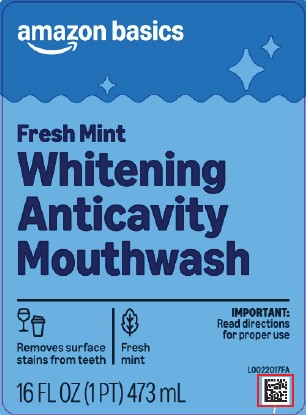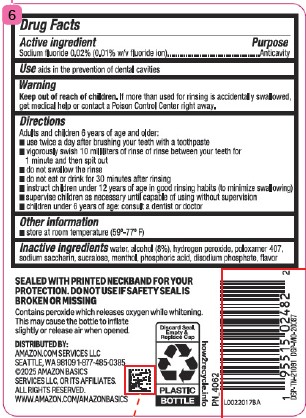 DRUG LABEL: Anticavity
NDC: 72288-439 | Form: MOUTHWASH
Manufacturer: Amazon.com Services LLC
Category: otc | Type: HUMAN OTC DRUG LABEL
Date: 20250915

ACTIVE INGREDIENTS: SODIUM FLUORIDE 0.2 mg/1 mL
INACTIVE INGREDIENTS: WATER; ALCOHOL; HYDROGEN PEROXIDE; POLOXAMER 407; SACCHARIN SODIUM; SUCRALOSE; MENTHOL; PHOSPHORIC ACID; SODIUM PHOSPHATE, DIBASIC, ANHYDROUS

Basics 435.000/435AA
Anticavity Whitening Rinse

Active Ingredient

Sodium fluoride 0.02% (0.01% w/v fluoride ion)

Purpose

Anticavity

Use

Aids in the prevention of dental cavities

Warnings

for this product

Keep out of reach of children.

If more than used for rinsing is accidentally swallowed, get medical help or contact a Poison Control Center right away.

Directions

Adults and children 6 years of age and older:

- use twice a day after brushing your teeth with a toothpaste
- vigorously swish 10 milliliters of rinse between your teeth for 1 minute and then spit out
- do not swallow the rinse
- do not eat or drink for 30 minutes after rinsing
- instruct children under 12 years of age in good rinsing habits (to minimize swallowing)
- supervise children as necessary until capable of using without supervision
- children under 6 years of age: consult a dentist or doctor

Inactive ingredients

water, alcohol (8%), hydrogen peroxide, poloxamer 407, sodium saccharin, sucralose, menthol, phosphoric acid, disodium phosphate, flavor

Other information

store at room temperature (59º-77ºF)

Tamper Evident Statement

SEALED WITH PRINTED NECKBAND FOR YOUR PROTECTION

DO NOT USE IF SAFETY SEAL IS BROKEN OR MISSING

Claims

Contains peroxide which releases oxygen while whitening.

This may cause the bottle to inflate slightly or release air when opened.

ADVERSE REACTIONS

DISTRIBUTED BY:

Amazon.com Services, LLC

Seattle, WA 98109 1-877-485-0385

© 2025 Amazon Basics Services LLC, or its affiliates.

All rights reserved.

www.amazon.com/amazonbasics

Discard Seal, Empty & Replace Cap

PLASTIC BOTTLE

how2recycle.info

DSP-TN-21091 DSP-MO-20087

principal display panel

amazon basics

Fresh Mint

Whitening

Anticavity

Mouthwash

Removes surface stains from teeth

Fresh Mint

IMPORTANT: READ DIRECTIONS FOR PROPER USE

16 FL OZ (1 PT) 473 mL